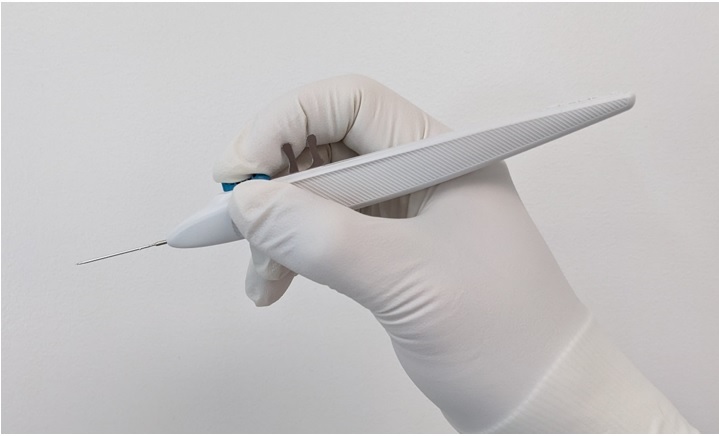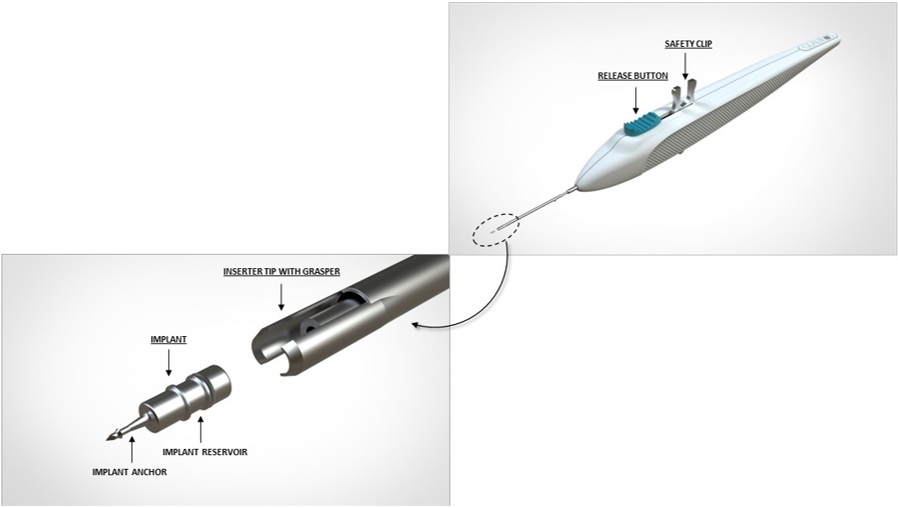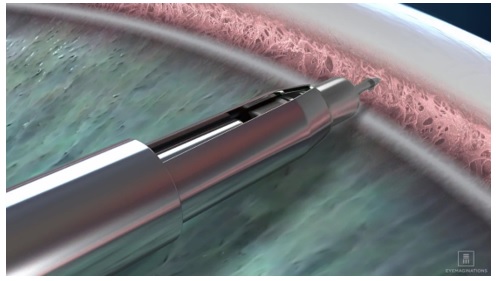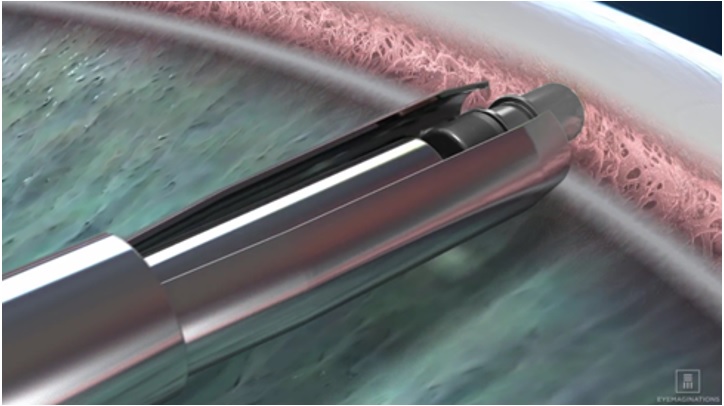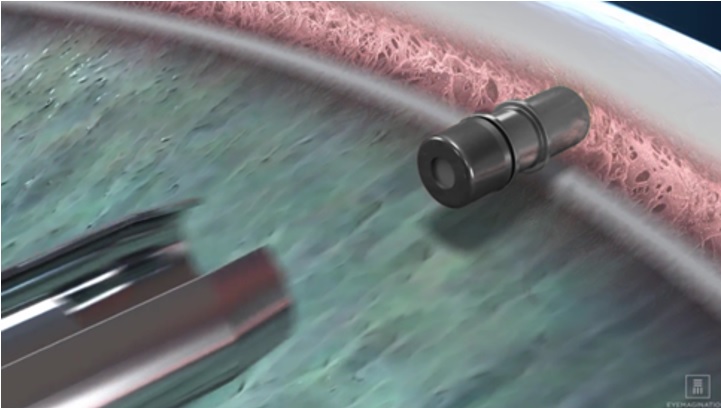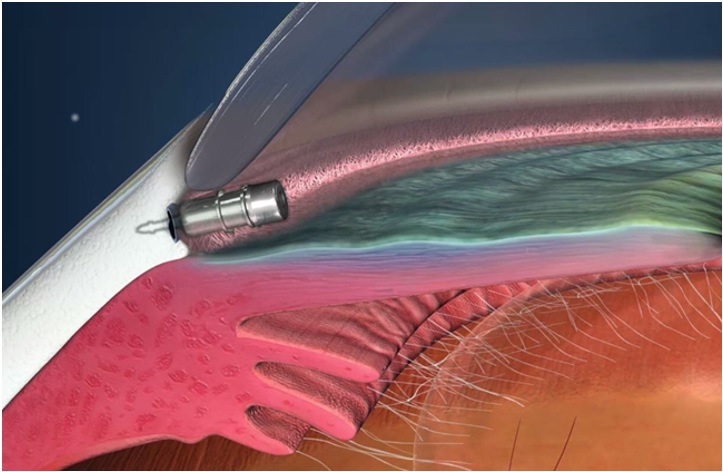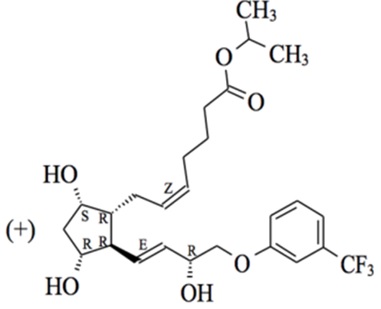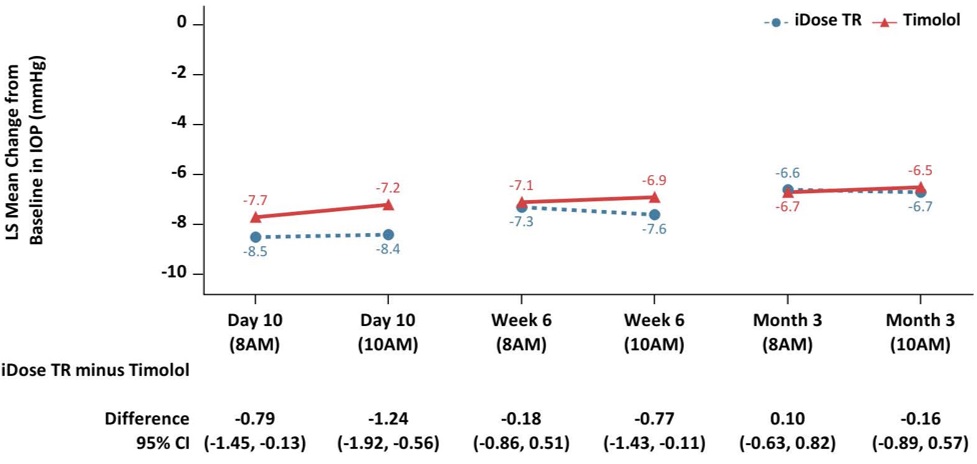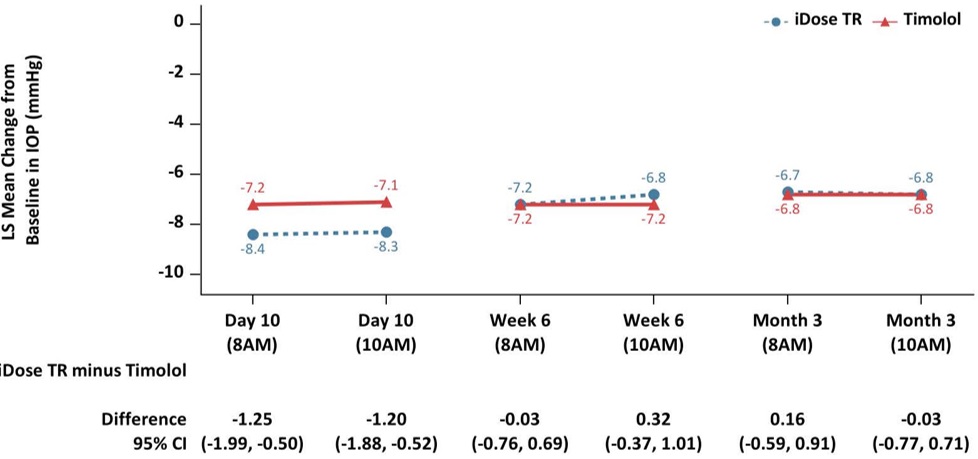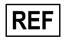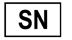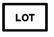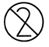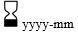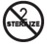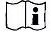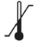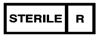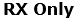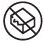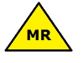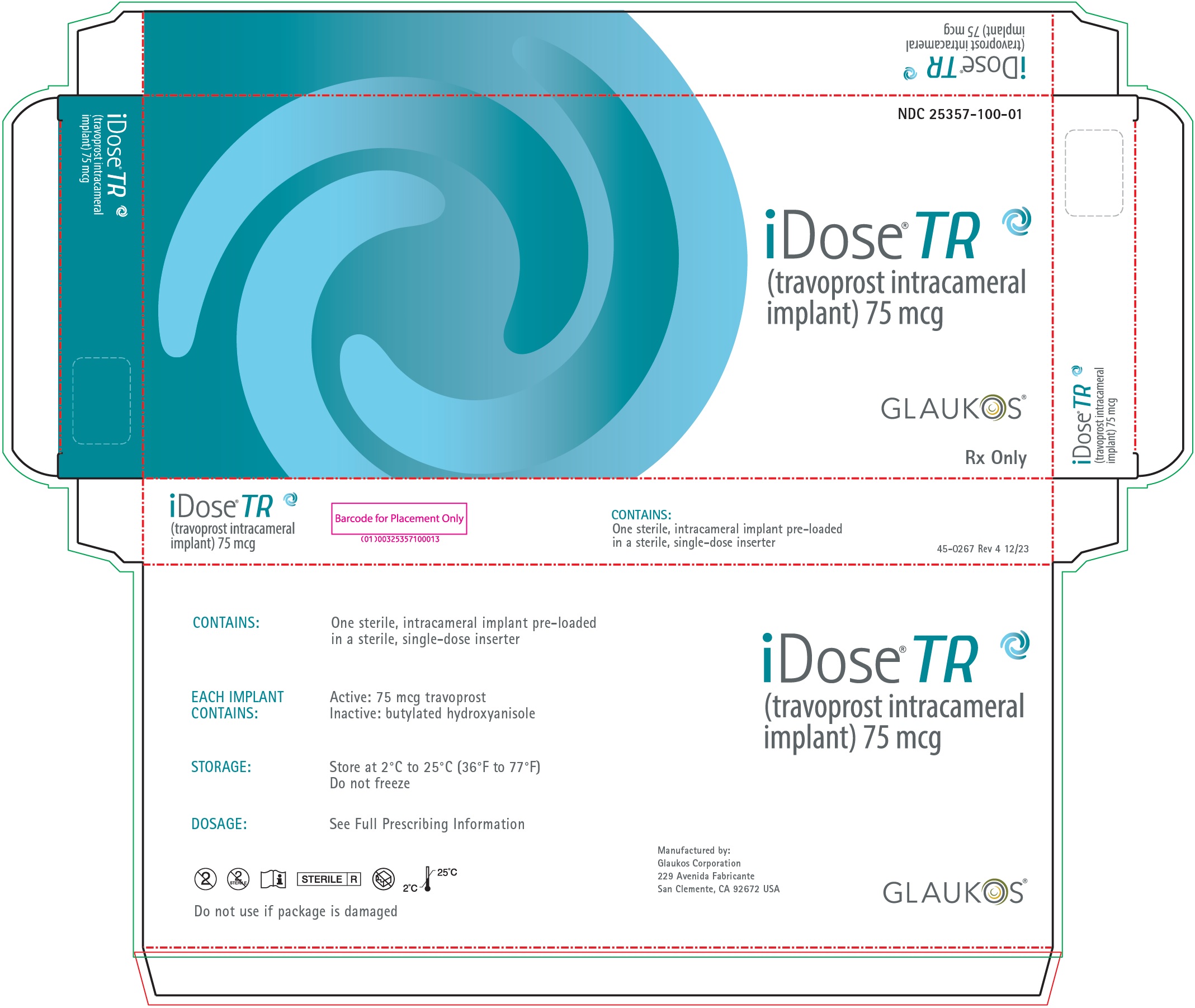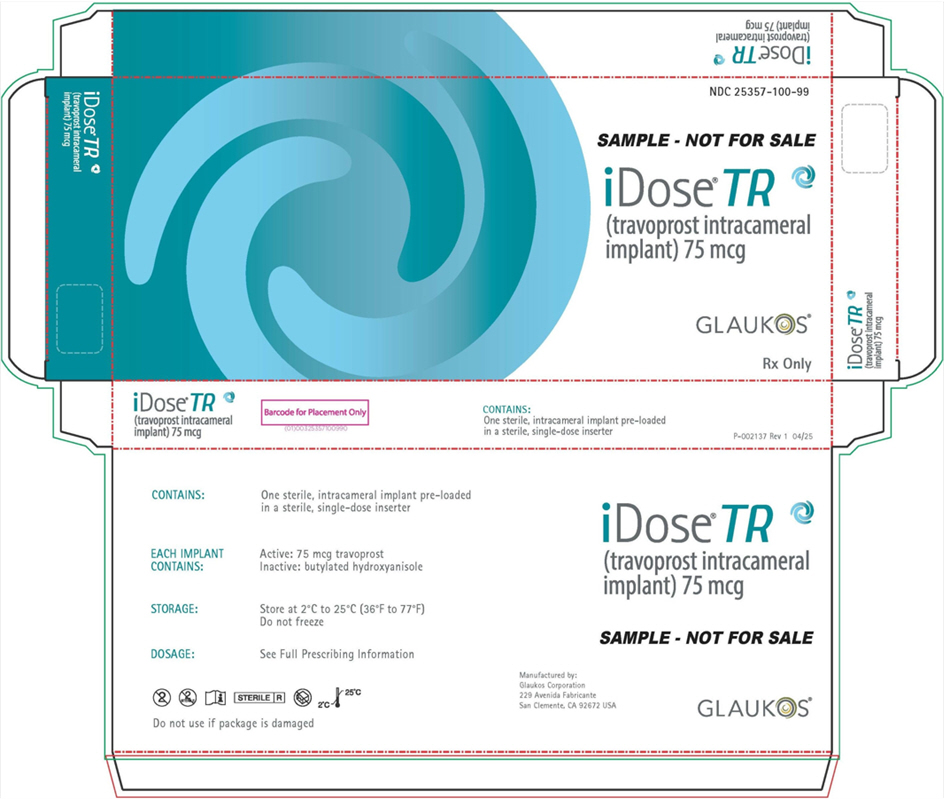 DRUG LABEL: iDose TR
NDC: 25357-100 | Form: IMPLANT
Manufacturer: Glaukos Corporation
Category: prescription | Type: HUMAN PRESCRIPTION DRUG LABEL
Date: 20260204

ACTIVE INGREDIENTS: TRAVOPROST 75 ug/1 1

HIGHLIGHTS OF PRESCRIBING INFORMATION

These highlights do not include all the information needed to use iDose® TR safely and effectively. See full prescribing information for iDose® TR.
iDose® TR (travoprost intracameral implant), for intracameral administration
Initial U.S. Approval: 2001

RECENT MAJOR CHANGES

Dosage and Administration (2.1, 2.2, 2.3, 2.4, 2.5) | 1/2026
Warnings and Precautions (5.3, 5.4, 5.5) | 1/2026

1 INDICATIONS AND USAGE

iDose® TR is a prostaglandin analog indicated for the reduction of intraocular pressure (IOP) in patients with open-angle glaucoma (OAG) or ocular hypertension (OHT) (1)

2 DOSAGE AND ADMINISTRATION

- For ophthalmic intracameral administration (2.1)
- The intracameral administration should be carried out under standard aseptic conditions (2.2)

3 DOSAGE FORMS AND STRENGTHS

Intracameral implant containing 75 mcg travoprost, pre-loaded in a single-dose inserter (3)

4 CONTRAINDICATIONS

- Ocular or periocular infections (4.1)
- Corneal endothelial dystrophy (4.2)
- Prior corneal transplantation (4.3)
- Hypersensitivity (4.4)

5 WARNINGS AND PRECAUTIONS

- Iridocorneal Angles: iDose TR should be used with caution in patients with narrow angles or other angle abnormalities (5.1)
- Device Dislocation: Monitor patients routinely to confirm the location of the iDose TR at the site of administration (5.2)
- Pigmentation: Increased pigmentation of the iris can occur. Iris pigmentation is likely to be permanent (5.8)

6 ADVERSE REACTIONS

In controlled studies, the most common ocular adverse reactions reported in 2% to 6% of patients were increases in intraocular pressure, iritis, dry eye, and visual field defects (6.1)

To report SUSPECTED ADVERSE REACTIONS, contact Glaukos Corporation at 1-888-404-1644 or FDA at 1-800-FDA-1088 or www.fda.gov/medwatch.

FULL PRESCRIBING INFORMATION

1 INDICATIONS AND USAGE

iDose® TR (travoprost intracameral implant) is indicated for the reduction of intraocular pressure (IOP) in patients with open-angle glaucoma (OAG) or ocular hypertension (OHT).

2 DOSAGE AND ADMINISTRATION

2.1 General Dosing Information

iDose TR is a travoprost delivery system consisting of a travoprost releasing implant pre-loaded in a sterile, single-dose inserter. iDose TR is administered intracamerally through a small, clear corneal incision and is anchored into the sclera at the iridocorneal angle.

2.2 Administration Instructions

1. The procedure must be carried out under aseptic conditions which include use of sterile gloves and a sterile drape.
2. The eye should be anesthetized using general, retrobulbar, peribulbar, or topical anesthesia per standard operating room procedures.
3. The iDose TR implantation procedure must be performed under magnification that allows clear visualization of the anterior chamber angle and angle structures including trabecular meshwork, with the patient's head in a stabilized position. The pupil should not be dilated prior to the procedure.
4. An intracameral miotic can be injected to deepen the angle prior to insertion of the iDose TR.
5. It is recommended that the implant surgery be performed from the temporal side, using a temporal clear corneal incision. The implant will be implanted through the angle and the trabecular meshwork into the sclera on the nasal side.
6. Remove the barrier pouch from the carton and examine for damage. Open the barrier pouch, discard the oxygen scavenger packet, and remove the blister tray with Tyvek® lid. Open the Tyvek lid containing the iDose TR pre-loaded inserter and present to the surgeon. The iDose TR implant and single-dose inserter should be handled in the sterile field. Caution: Do not use the iDose TR if the Tyvek lid has been opened or the packaging appears damaged.
7. Prepare for gonioscopy by turning the patient's head away from the surgeon by approximately 15° to 25° and tilt the scope toward the surgeon by approximately 35°. The total combined angle should be approximately 50° to 60°.
8. Place a small amount of viscoelastic on the cornea. Position the gonioprism on the cornea using light touch gonioscopy. Adjust the microscope to locate and focus on the trabecular meshwork.
9. Inspect the angle with a gonioprism to ensure that a good view of all angle structures is available at the nasal implant location.
10. Hold the single-dose inserter with your index finger comfortably on the implant release button (see Figure 1)

Figure 1

11. Perform a detailed inspection of the tip of the sterile inserter under magnification to ensure that the iDose TR implant is present (see Figure 2).

Figure 2

12. Create a clear corneal incision of approximately 2.4 mm at the temporal limbus location using an instrument of the surgeon's choice.
13. Add a cohesive viscoelastic to the anterior chamber as needed to form the anterior chamber and improve visualization of the angle. Be careful not to overinflate.
14. Insertion of the implant:
a. When ready for implantation, remove the safety clip which holds the release button in place by squeezing and rocking the clip backwards (see Figure 2). Place finger on the release button to ensure it remains in the forward position and does not prematurely release the implant.
b. To smoothly enter the anterior chamber, slide the inserter tip with implant "side to side" in the incision.
c. Advance to the pupillary margin and ensure there is sufficient cohesive viscoelastic on the cornea before replacing the gonioprism onto the cornea.
d. Take care to avoid contact with the lens or cornea.
e. Advance to the anterior chamber angle and approach the trabecular meshwork (see Figure 3).

Figure 3
f. Press the implant directly through the trabecular meshwork, compressing the tissue until the implant anchor securely penetrates the sclera through the back wall of Schlemm's canal. The base of the implant reservoir should be firmly in contact with and compressing the trabecular meshwork.
g. Once the anchor of the implant is securely embedded in sclera, pause for the tissue to relax. Carefully slide the implant release button backwards to open the inserter tip with grasper and release the implant from the inserter (see Figure 4a). Ensuring the implant has released from the inserter grasper, slowly remove the inserter straight back (see Figure 4b). Avoid pulling the implant out of position.

Figure 4a

Figure 4b

h. Apply slight pressure to the sides of the implant with the tip of the inserter to ensure the implant is fully anchored into scleral tissue. Note: If for any reason the implant appears loose or disengaged from the scleral tissue after the initial implantation, slide the implant release button back to fully open the graspers. Position the graspers between the ribs on the implant and regrasp the body of the implant between the ribs by pushing the release button forward and re-implant a minimum of ½ clock hour to either side. Do not re-implant at the same location.
i. Withdraw the inserter from the eye.
15. Location of iDose TR in Trabecular Meshwork
a. Perform a high-magnification examination to confirm that the implant is in proper position (i.e., the proximal end rests in the anterior chamber with an unobstructed membrane) (see Figure 5) and securely attached with the anchor thoroughly embedded in the sclera.

Figure 5

b. It is normal for an edge of the implant to make contact with the iris. Note: In a normal iris (no viscoelastic in the anterior chamber and non-constricted pupil), the iris may obstruct the view of a portion of the cap of the implant.
c. Irrigate and aspirate the anterior chamber with balanced salt solution to remove all viscoelastic. Press down on the posterior edge of the incision as needed to facilitate complete removal of viscoelastic.
d. Inflate the anterior chamber with saline solution as needed to achieve physiologic pressure.

2.3 Evaluation and Testing Before Readministering iDose TR

Perform specular microscopy to evaluate the corneal endothelium and establish pre-implantation baseline corneal endothelial cell density prior to the initial administration of iDose TR and prior to each readministration [see Warnings and Precautions (5.4)].

Table 1 describes readministration modifications if specific adverse reactions have occurred [see Contraindications (4), Warnings and Precautions (5.2, 5.5)].

Table 1: Dosage (Readministration) Modifications for Adverse Reactions
Adverse Reactions | Dosage Modification
Ocular or periocular infections | Withhold dose (readministration)
Prior iDose TR device dislocation | Withhold dose (readministration)
Central corneal endothelial cell loss of 10% or greater from pre-administration baseline (adjusted for age-related 1% loss per year and for a 10% loss following an anterior segment surgical procedure [e.g., cataract surgery]) | Withhold dose (readministration)

2.4 Readministration Instructions

Note: When readministering an iDose TR implant, always remove the previous iDose TR implant AFTER implantation of the new implant.

1. Follow "Administration Instructions" Steps 1 to 13 [see Dosage and Administration (2.2)].
2. Assure the anterior chamber is fully formed with a cohesive viscoelastic. If you notice a soft eye, or a shallow anterior chamber, re-inflate. If needed, apply cohesive viscoelastic directly on the previous implant while inflating to remove any loose tissue, iris strands, or debris.
3. Insert the new iDose TR implant following "Administration Instructions" Step 14a through 14h [see Dosage and Administration (2.2)].
4. With the iDose TR inserter or viscoelastic cannula, perform a procedural check on the previous implant by gently touching it left to right, right to left, and bottom to top (iris up). Movement of the iris is suggestive of adhesions to the implant.
5. If the previous iDose TR is adhered to the iris, slide the release button on the inserter back to fully open the graspers. Position the graspers between the ribs on the implant and regrasp the body of the implant between the ribs by pushing the release button forward. Slowly rotate the grasped implant 10° clockwise and counterclockwise. Any movement of the iris is suggestive of adhesions. Gently twist and separate the implant from any adhesions while slowly removing the implant.
6. When satisfied that the previous iDose TR is free and clear of the iris, slowly pull the previous implant back from the trabecular meshwork avoiding tension on adjacent ocular structures and withdraw the inserter from the eye.
7. Follow "Administration Instructions" Step 15 [see Dosage and Administration (2.2)].

2.5 Frequency of Readministration

It is not recommended to readminister an iDose TR more than once per year.

3 DOSAGE FORMS AND STRENGTHS

Intracameral implant containing 75 mcg travoprost, pre-loaded in a single-dose inserter.

4 CONTRAINDICATIONS

4.1 Ocular or Periocular Infections

iDose TR (travoprost intracameral implant) is contraindicated in patients with active or suspected ocular or periocular infections.

4.2 Corneal Endothelial Dystrophy

iDose TR is contraindicated in patients with corneal endothelial cell dystrophy (e.g., Fuch's Dystrophy, corneal guttatae).

4.3 Prior Corneal Transplantation

iDose TR is contraindicated in patients with prior corneal transplantation, or endothelial cell transplants (e.g., Descemet's Stripping Automated Endothelial Keratoplasty [DSAEK]).

4.4 Hypersensitivity

iDose TR is contraindicated in patients with hypersensitivity to travoprost or to any other components of the product.

5 WARNINGS AND PRECAUTIONS

5.1 Iridocorneal Angles

iDose TR should be used with caution in patients with narrow iridocorneal angles (Shaffer grade < 3) or other angle abnormalities (e.g., peripheral anterior synechia, rubeosis iridis) that could impair proper placement of iDose TR at the planned implantation site.

5.2 Device Dislocation

Dislocation of the iDose TR has been observed in clinical trials. Patients should be monitored routinely to confirm the location of the iDose TR at the site of administration. If the iDose TR implant becomes dislocated, it should be surgically removed [see Dosage and Administration (2.3, 2.4)].

5.3 Patients without Baseline Corneal Endothelial Cell Density Prior to Initial Administration

It is not recommended to readminister iDose TR if baseline central corneal endothelial cell density was not established prior to initial administration of iDose TR [see Warnings and Precautions (5.4, 5.5)].

5.4 Recommended Minimum Corneal Endothelial Cell Density for Readministration

Central corneal endothelial cell density should not be less than the recommended minimum listed in Table 2 prior to the initial administration of iDose TR and prior to each readministration.

If corneal endothelial cell density was not established prior to the initial administration of iDose TR and only a single eye was implanted, corneal endothelial cell density in the un-implanted contralateral eye meeting the recommended minimum density may be used for eligibility determination for readministration of iDose TR (see Table 2).

Table 2: Recommended Minimum Central Corneal Endothelial Cell Density
 | Central Corneal Endothelial Cell Density
Age | Phakic Eyes | Pseudophakic Eyes
≤ 45 years | 2,200 (cells/mm^2) | 1,540 (cells/mm^2)
46 to 55 years | 2,000 (cells/mm^2) | 1,400 (cells/mm^2)
56 to 65 years | 1,800 (cells/mm^2) | 1,260 (cells/mm^2)
> 65 years | 1,600 (cells/mm^2) | 1,120 (cells/mm^2)

5.5 Corneal Endothelial Cell Loss

iDose TR should be readministered with caution in eyes with 10% or greater loss in central corneal endothelial cell density from pre-administration baseline (adjusted for age-related 1% loss per year and for a 10% loss following an anterior segment surgical procedure [e.g., cataract surgery]).

If baseline corneal endothelial cell density was not established prior to the initial administration of iDose TR and only a single eye is implanted, a 10% threshold level of endothelial cell density loss as a difference of the implanted eye versus un-implanted contralateral eye should be considered before readministering iDose TR.

5.6 Macular Edema

Macular edema, including cystoid macular edema, has been reported during treatment with ophthalmic travoprost, including iDose TR intracameral implant. iDose TR should be used with caution in aphakic patients, in pseudophakic patients with a torn posterior lens capsule, or in patients with known risk factors for macular edema.

5.7 Intraocular Inflammation

Prostaglandin analogs, including iDose TR, have been reported to cause intraocular inflammation. iDose TR should be used with caution in patients with active intraocular inflammation (e.g., uveitis) because the inflammation may be exacerbated.

5.8 Pigmentation

Topical ophthalmic travoprost has been reported to cause increased pigmentation to pigmented tissues. Pigmentation is expected to increase as long as travoprost is administered. The pigmentation change is due to increased melanin content in the melanocytes rather than to an increase in the number of melanocytes. After discontinuation of travoprost, pigmentation of the iris is likely to be permanent. The long-term effects of increased pigmentation are not known.

Iris color change may not be noticeable for several months to years. Typically, the brown pigmentation around the pupil spreads concentrically towards the periphery of the iris and the entire iris or parts of the iris become more brownish. Neither nevi nor freckles of the iris appear to be affected by treatment. While treatment with travoprost can be continued in patients who develop noticeably increased iris pigmentation, these patients should be examined regularly.

5.9 Endophthalmitis

Intraocular surgical procedures and injections have been associated with endophthalmitis. Proper aseptic technique must always be used with administering iDose TR, and patients should be monitored following the administration.

5.10 Magnetic Resonance Imaging (MRI) Conditional

iDose TR is MR Conditional. Patients should be informed that the implant is MR Conditional (as noted on their Patient ID card). If the patient requires magnetic resonance imaging (MRI), they should inform their healthcare provider that they have an iDose TR implanted in their eye.

A patient with the iDose TR may be safely scanned under the following conditions. Failure to follow these conditions may result in injury to the patient.

Parameter | Condition of Use / Information
Nominal Values of Static Magnetic Field (T) | 3.0 T or less
Maximum Spatial Field Gradient (T/m and gauss/cm) | 40-T/m (4,000-gauss/cm)
Type of RF Excitation | Circularly Polarized (CP) (i.e., Quadrature-Transmission)
Transmit RF Coil Information | Any transmit RF coil may be used
Operating Mode of MR System | Normal Operating Mode
Maximum Whole Body Averaged SAR | 2-W/kg (Normal Operating Mode)
Maximum Head SAR | 3.2-W/kg (Normal Operating Mode)
Limits on Scan Duration | Whole body averaged SAR of 2-W/kg for 60 minutes of continuous RF exposure (i.e., per pulse sequence or back-to-back sequences/series without breaks)
MR Image Artifact | The presence of this implant produces an imaging artifact. Therefore, carefully select pulse sequence parameters if the implant is located in the area of interest.

6 ADVERSE REACTIONS

The following adverse reactions are described elsewhere in the labeling:

- Ocular or periocular infections [see Contraindications (4.1)]
- Corneal endothelial dystrophy [see Contraindications (4.2)]
- Prior corneal transplantation [see Contraindications (4.3)]
- Hypersensitivity [see Contraindications (4.4)]
- Device dislocation [see Warnings and Precautions (5.2)]
- Macular edema [see Warnings and Precautions (5.6)]
- Intraocular inflammation [see Warnings and Precautions (5.7)]
- Pigmentation [see Warnings and Precautions (5.8)]
- Endophthalmitis [see Warnings and Precautions (5.9)]

6.1 Clinical Trials Experience

Because clinical trials are conducted under widely varying conditions, adverse reaction rates observed in the clinical trials of a drug cannot be directly compared to rates in the clinical trials of another drug and may not reflect the rates observed in practice.

The following adverse events rates are derived from three randomized, double-masked clinical trials in which 868 patients with open angle glaucoma (OAG) or ocular hypertension (OHT) received an iDose TR and were followed for one year. The most commonly reported ocular adverse reactions (2% to 6%) were increases in intraocular pressure, iritis, dry eye, visual field defects, eye pain, ocular hyperaemia, and reduced visual acuity. Ocular adverse reactions reported in less than 2% of patients were conjunctival hemorrhage, photophobia, punctate keratitis, blepharitis, eye irritation, corneal abrasion, device dislocation, vitreous detachment, and foreign body sensation in eyes.

8 USE IN SPECIFIC POPULATIONS

8.1 Pregnancy

Risk Summary

There are no adequate and well-controlled studies of iDose TR (travoprost intracameral implant) administration in pregnant women to inform a drug-associated risk. Subcutaneous administration of travoprost to pregnant mice and rats throughout the period of organogenesis produced embryo-fetal lethality, spontaneous abortion, and premature delivery at potentially clinically relevant doses.

Advise pregnant women of a potential risk to a fetus. iDose TR should be administered during pregnancy only if the potential benefit justifies the potential risk to the fetus.

Data

Animal Data

An embryo-fetal development study was conducted in pregnant rats administered travoprost once daily at doses up to 10 mcg/kg by subcutaneous injection from gestation day (GD) 6 to 17, to target the period of organogenesis. At 10 mcg/kg, 116 times the maximum human ocular dose (MHOD) of 1 implant per eye, based on body surface area (BSA), assuming sustained travoprost release from the implant for 6 months or 0.0139 mcg/kg/day, travoprost was teratogenic in rats, evidenced by an increase in the incidence of skeletal malformations as well as external and visceral malformations, including fused sternebrae, domed head and hydrocephaly. Travoprost caused post-implantation loss at 10 mcg/kg. The fetal no observed adverse effect level (NOAEL) was 3 mcg/kg (34.5 times the maximum human ocular dose (MHOD) of 1 implant per eye, based on BSA).

An embryo-fetal development study was conducted in pregnant mice administered travoprost once daily by subcutaneous injection at doses up to 1 mcg/kg from GD 6 to 16, to target the period of organogenesis. Travoprost induced an increase in post-implantation losses and a decrease in fetal viability in mice at subcutaneous doses > 0.3 mcg/kg. The fetal NOAEL was 0.3 mcg/kg (1.7 times the MHOD based on BSA). The maternal NOAEL was 1 mcg/kg (5.8 times the MHOD based on BSA).

Pre/postnatal development studies were conducted in rats administered travoprost once daily by subcutaneous injection from GD 7 (early embryonic period) to postnatal Day 21 (end of lactation period). At doses of greater than or equal to 0.12 mcg/kg/day (1.4 times the MHOD based on BSA), the incidence of post-natal mortality was increased, and neonatal body weight was decreased. Neonatal development was also affected, evidenced by delayed eye opening, pinna detachment and preputial separation, and by decreased motor activity.

8.2 Lactation

Risk Summary

There are no data on the effects of travoprost on the breastfed child or milk production. It is not known if travoprost is present in human milk following ophthalmic administration. The developmental and health benefits of breastfeeding should be considered, along with the mother's clinical need for iDose TR and any potential adverse effects on the breast-fed child from iDose TR.

8.4 Pediatric Use

The safety and effectiveness of iDose TR have not been established in pediatric patients.

8.5 Geriatric Use

No overall differences in safety or effectiveness have been observed between elderly and other adult patients.

11 DESCRIPTION

iDose TR (travoprost intracameral implant) is a sterile intracameral implant containing 75 mcg of travoprost. The intracameral implant consists of a titanium implant reservoir with a membrane controlling the sustained release of travoprost. The sterile implant is pre-loaded in a sterile single-dose inserter to facilitate insertion directly through the trabecular meshwork of the anterior chamber angle into the sclera.

Travoprost is a prostaglandin analog. Its chemical name is 5-heptenoic acid, 7-[(1R,2R,3R,5S)-3,5-dihydroxy-2-[(1E,3R)-3-hydroxy-4-[3-(trifluoromethyl)phenoxy]-1-buten-1-yl]cyclopentyl]-, 1-methylethyl ester, (5Z)-. Travoprost has a molecular formula of C26H35F3O6 and a molecular weight of 500.55 g/mol.

The chemical structure of travoprost is:

Travoprost is a clear, colorless to slightly yellow oil that is very soluble in acetonitrile, methanol, octanol, and chloroform. It is practically insoluble in water.

12 CLINICAL PHARMACOLOGY

12.1 Mechanism of Action

Travoprost free acid, a prostaglandin analog is a selective FP prostanoid receptor agonist, which is believed to reduce IOP by increasing uveoscleral outflow. The exact mechanism of action is unknown at this time.

12.3 Pharmacokinetics

Travoprost, an isopropyl ester prodrug, is hydrolyzed by esterases in the cornea and other intraocular tissues to its biologically active free acid. Systemically, travoprost free acid is metabolized to inactive metabolites via beta-oxidation of the α (carboxylic acid) chain to give the 1,2-dinor and 1,2,3,4-tetranor analogs, via oxidation of the 15-hydroxyl moiety, as well as via reduction of the 13, 14 double bond.

Data from a pharmacokinetic study of 105 subjects evaluating two models of the travoprost intracameral implant with different elution rates have shown that the plasma concentrations of travoprost free acid are below 10 pg/mL (the quantitation limit of the assay, LLOQ) in all subjects at day 10, week 12 and month 12 following administration of iDose TR.

13 NONCLINICAL TOXICOLOGY

13.1 Carcinogenesis, Mutagenesis, Impairment of Fertility

Carcinogenesis

Two-year carcinogenicity studies in mice and rats at subcutaneous doses of 10, 30, or 100 mcg/kg/day did not show any evidence of carcinogenic potential. However, at 100 mcg/kg/day, male rats were only treated for 82 weeks, and the maximum tolerated dose (MTD) was not reached in the mouse study. The high dose (100 mcg/kg) represents > 500 times the MHOD based on BSA.

Mutagenesis

Travoprost was not mutagenic in the Ames test, mouse micronucleus test or rat chromosome aberration assay. A slight increase in the mutant frequency was observed in one of two mouse lymphoma assays in the presence of rat S-9 activation enzymes.

Fertility

Travoprost did not affect mating or fertility indices in male or female rats at subcutaneous doses up to 10 mcg/kg/day (116 times the MHOD based on BSA) At 10 mcg/kg/day (116 times the MHOD based on BSA), the mean number of corpora lutea was reduced, and the post-implantation losses were increased. These effects were not observed at 3 mcg/kg/day (34.5 times the MHOD based on BSA).

14 CLINICAL STUDIES

iDose TR was evaluated in two multicenter, 12-month, randomized, parallel-group, double-masked, controlled clinical trials in patients with OAG or OHT. In both trials (GC-010, NCT03519386, and GC-012, NCT03868124), iDose TR was compared to twice-daily topical administration of timolol maleate ophthalmic solution, 0.5%. In the first 3 months following administration, iDose TR demonstrated an IOP change from baseline of -6.6 to -8.4 mmHg in the study eye of patients with a mean baseline IOP of 24 mmHg (see Figure 6).

Figure 6: Change from Baseline in Study Eye IOP (mmHg) and Treatment Difference

Study GC-010

Study GC-012

iDose TR demonstrated non-inferiority to timolol ophthalmic solution in IOP reduction during the first 3 months. Subsequently, iDose TR did not demonstrate non-inferiority over the next 9 months.

16 HOW SUPPLIED/STORAGE AND HANDLING

iDose TR (travoprost intracameral implant) (NDC 25357-100-01) is provided sterile and pre-loaded in a sterile, single-dose inserter that is packaged in a blister tray sealed with a Tyvek lid. Implants are individually serialized and the serial number is provided on the tray lid.

The tray is sealed inside of a transparent plastic pouch along with an oxygen scavenger packet, which is packaged inside a unit carton. Tamper evidence is provided by a seal on both ends of the carton.

Storage:

Store at 2°C to 25°C (36°F to 77°F). Do not freeze.

17 PATIENT COUNSELING INFORMATION

Intraocular Inflammation or Endophthalmitis
Advise patients about the potential risk for complications including, but not limited to, the development of intraocular inflammation or endophthalmitis [see Warnings and Precautions (5.6, 5.7, 5.9)].

Potential for Pigmentation
Advise patients about the potential for increased brown pigmentation of the iris, which may be permanent [see Warnings and Precautions (5.8)].

MR Conditional
Advise patients that the implant is MR Conditional (as noted on their Patient ID card), and that if they require magnetic resonance imaging (MRI), they should inform their healthcare provider that they have iDose TR implanted in their eye [see Warnings and Precautions (5.10)].

When to Seek Physician Advice
Advise patients that if the eye becomes red, sensitive to light, painful, or develops a change in vision, they should seek immediate care from an ophthalmologist [see Warnings and Precautions (5.2, 5.7, 5.9)].

Symbols that are included in the labeling of this product.

Symbol

Definition

Catalogue/Model Number

Serial Number

Lot Number

Do not re-use

Use-by date (year-month)

Do not resterilize

See package insert for Full
Prescribing Information

Temperature limit

Sterilized by e-beam irradiation

For prescription use only

Do not use if package is damaged

MR Conditional

Manufactured by Glaukos Corp., 229 Avenida Fabricante, San Clemente, CA 92672
© 2026 Glaukos. All rights reserved.
Glaukos and iDose are registered trademarks of Glaukos Corporation. All other trademarks are the property of their respective owners.

Patents www.glaukos.com/patents

P-000992 Rev 2

PRINCIPAL DISPLAY PANEL - NDC: 25357-100-01 - 75 mcg Carton Labeling - Physician Sample

NDC 25357-100-99

SAMPLE - NOT FOR SALE

iDose® TR
(travoprost intracameral
implant) 75 mcg

GLAUKOS®

Rx Only